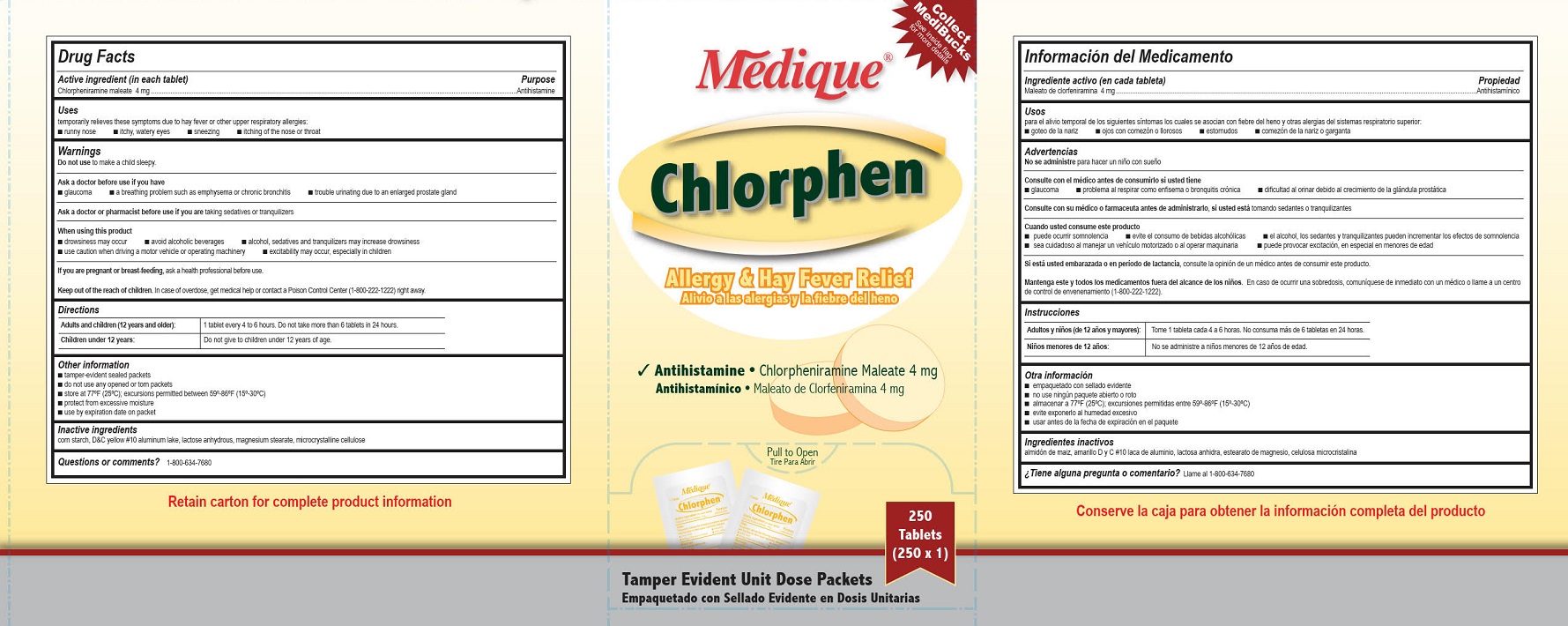 DRUG LABEL: Medique Chlorphen
NDC: 47682-169 | Form: TABLET
Manufacturer: Unifirst First Aid Corporation
Category: otc | Type: HUMAN OTC DRUG LABEL
Date: 20250908

ACTIVE INGREDIENTS: CHLORPHENIRAMINE MALEATE 4 mg/1 1
INACTIVE INGREDIENTS: STARCH, CORN; ANHYDROUS LACTOSE; CELLULOSE, MICROCRYSTALLINE; MAGNESIUM STEARATE; D&C YELLOW NO. 10 ALUMINUM LAKE

Medique Chlorphen

Active ingredient (in each tablet)

Chlorpheniramine maleate 4 mg

Purpose

Antihistamine

Uses

temporarily relieves these symptoms due to hay fever or other upper respiratory allergies:

■ runny nose

■ itchy, watery eyes

■ sneezing

■ itching of the nose or throat

Warnings

Do not use to make a child sleepy.

Ask a doctor before use if you have

■ glaucoma

■ a breathing problem such as emphysema or chronic bronchitis

■ trouble urinating due to an enlarged prostate gland

Ask a doctor or pharmacist before us if you are taking sedatives or tranquilizers.

When using this product

■ drowsiness may occur

■ avoid alcoholic beverages

■ alcohol, sedatives and tranquilizers may increase drowsiness

■ use caution when driving a motor vehicle or operating machinery

■ excitability may occur, especially in children

PREGNANCY OR BREAST FEEDING

If you are pregnant or breast-feeding, ask a health professional before use.

KEEP OUT OF REACH OF CHILDREN

Keep out of the reach of children. In case of overdose, get medical help or contact a Poison Control

Center (1-800-222-1222) right away.

Directions

Adults and children (12 years and older): 1 tablet every 4 to 6 hours. Do not take more than 6 tablets in 24 hours.

Children under 12 years: Do not give to children under 12 years of age

Other information

■ tamper evident sealed packets

■ do not use any opened or torn packets

■ store at 77°F (25°C); excursions permitted between 59º-86ºF (15º-30ºC)

■ protect from excessive moisture

■ use by expiration date on packet

Inactive ingredients

corn starch, D&C yellow #10 aluminum lake, lactose anhydrous, magnesium stearate, microcrystalline cellulose

Questions or comments? Call 1-800-634-7680

Medique Chlorpen Label

Medique ®

Chlorphen

Allergy and Hay Fever Relief

Alivio a las algergias y la fiebre del heno

Antihistamine • Chlorpheniramine Maleate 4mg

Antihistminico • Maleato de Clorfeniramina 4mg

Pull To Open

Tire Para Abrir

250 Tablets

(250 x 1)

Tamper Evident Unit Dose Packets

Empaquetado con Sellado Evidente en Dosis Unitarias